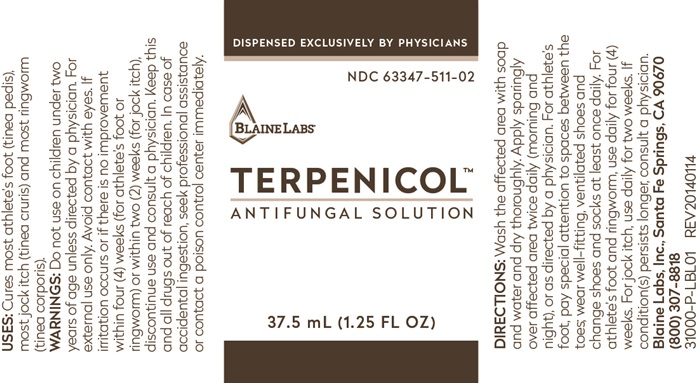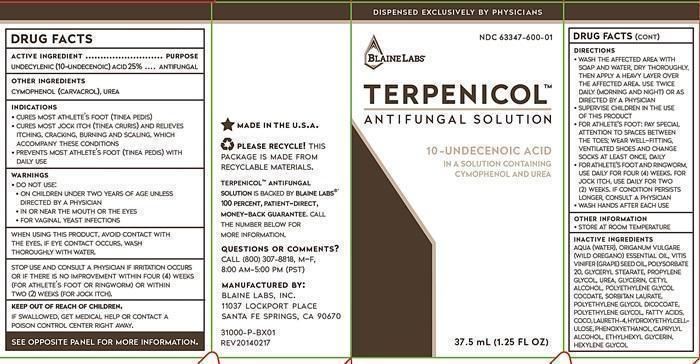 DRUG LABEL: TERPENICOL
NDC: 63347-600 | Form: LIQUID
Manufacturer: Blaine Labs Inc.
Category: otc | Type: HUMAN OTC DRUG LABEL
Date: 20231221

ACTIVE INGREDIENTS: UNDECYLENIC ACID 25 g/100 mL
INACTIVE INGREDIENTS: WATER; OREGANO LEAF OIL; GRAPE SEED OIL; POLYSORBATE 20; GLYCERYL MONOSTEARATE; PROPYLENE GLYCOL; UREA; GLYCERIN; CETYL ALCOHOL; PEG-7 GLYCERYL COCOATE; SORBITAN MONOLAURATE; POLYETHYLENE GLYCOL; COCONUT ACID; LAURETH-4; HYDROXYETHYL CELLULOSE (140 MPA.S AT 5%); PHENOXYETHANOL; CAPRYLIC ALCOHOL; ETHYLHEXYLGLYCERIN; HEXYLENE GLYCOL

ACTIVE INGREDIENT

DRUG FACTS
ACTIVE INGREDIENT
UNDECYLENIC (10-UNDECENOIC) ACID

PURPOSE

ANTIFUNGAL

KEEP OUT OF REACH OF CHILDREN

IF SWALLOWED, GET MEDICAL HELP OR CONTACT A POISON CONTROL CENTER RIGHT AWAY.

INDICATIONS

- CURES MOST ATHLETE'S FOOT (TINEA PEDIS)
- CURES MOST JOCK ITCH (TINEA CRURIS) AND RELIEVES ITCHING, CRACKING, BURNING AND SCALING, WHICH ACCOMPANY THESE CONDITIONS
- PREVENTS MOST ATHLETE'S FOOT (TINEA PEDIS) WITH DAILY USE

WARNINGS

- DO NOT USE:
- ON CHILDREN UNDER 2 YEARS OF AGE UNLESS DIRECTED BY A PHYSICIAN
- IN OR NEAR THE MOUTH OR THE EYES
- FOR VAGINAL YEAST INFECTIONS

WHEN USING THIS PRODUCT,

AVOID CONTACT WITH THE EYES. IF EYE CONTACT OCCURS, WASH THOROUGHLY WITH WATER.

STOP USE AND CONSULT A PHYSICIAN

IF IRRITATION OCCURS OR IF THERE IS NO IMPROVEMENT WITHIN FOUR (4) WEEKS (FOR ATHLETE'S FOOT OR RINGWORM) OR WITHIN TWO (2) WEEKS (FOR JOCK ITCH)..

DIRECTIONS

- WASH THE AFFECTED AREA WITH SOAP AND WATER, DRY THOROUGHLY, THEN APPLY A HEAVY LAYER OVER THE AFFECTED AREA. USE TWICE DAILY (MORNING AND NIGHT) OR AS DIRECTED BY A PHYSICIAN
- SUPERVISE CHILDREN IN THE USE OF THIS PRODUCT
- FOR ATHLETE'S: PAY SPECIAL ATTENTION TO SPACES BETWEEN TOES ; WEAR WELL-FITTING, VENTILATED SHOES AND CHANGE SOCKS AT LEAST ONCE, DAILY
- FOR ATHLETE'S FOOT AND RINGWORM, USE DAILY FOR FOUR (4) WEEKS. FOR JOCK ITCH, USE DAILY FOR TWO (2) WEEKS. IF CONDITION PERSISTS LONGER, CONSULT A PHYSICIAN
- WASH HANDS AFTER EACH USE

OTHER INFORMATION

- STORE AT ROOM TEMPERATURE

INACTIVE INGREDIENTS OTHER INGREDIENTS

CYMOPHENOL (CARVACROL), UREA, AQUA (WATER), ORGANIC VULGARE (WILD OREGANO) ESSENTIAL OIL, VITIT VINFER (GRAPE) SEED OIL, POLYSORBATE 20, GLYCERYL STEARATE, PROPYLENE GLYCOL, UREA, GLYCERIN, CETYL ALCOHOL, POLYETHYLENE GLYCOL COCOATE, SORBITAN LAURATE, POLYETHYLENE GLYCOL DICOCOATE, POLYETHYLENE GLYCOL, FATTY ACIDS, COCO, LAURETH-4, HYDROXYETHYLCELLULOSE, PHENOXYETHANOL CAPRYLY ALCOHOL, ETHYLHEXYL GLYCERIN, HEXYLENE GLYCOL

TERPENICOL PRODUCT LABEL LABEL BOX

DISPENSED EXCLUSIVELY BY PHYSICIANS

NDC 63347-600-01

BLAINE LABS®

TERPENICOL™

ANTIFUNGAL SOLUTION

10-UNDECENOIC ACID

IN A SOLUTION CONTAINING CYMOPHENOL AND UREA

37.5 mL (1.25 FL OZ)

SEE OPPOSITE PANEL FOR MORE INFORMATION.

* MADE IN THE U.S.A.

PLEASE RECYCLE! THIS PACKAGE IS MADE FROM RECYCLABLE MATERIALS.

TEPENICOL ANTIFUNGAL
SOLUTION IS BACKED BY BLAINE LABS®
100 PERCENT, PATIENT-DIRECT, MONEY-BACK GUARANTEE. CALL THE NUMBER BELOW FOR MORE INFORMATION.

QUESTIONS OR COMMENTS?
CALL (800) 307-8818, M-F, 8:00 AM - 5:00 pm (PST)

MANUFACTURED BY:
BLAINE LABS, INC.
11037 LOCKPORT PLACE
SANTE FE SPRINGS, CA 90670

31000-P-BX01
REV20140217

res